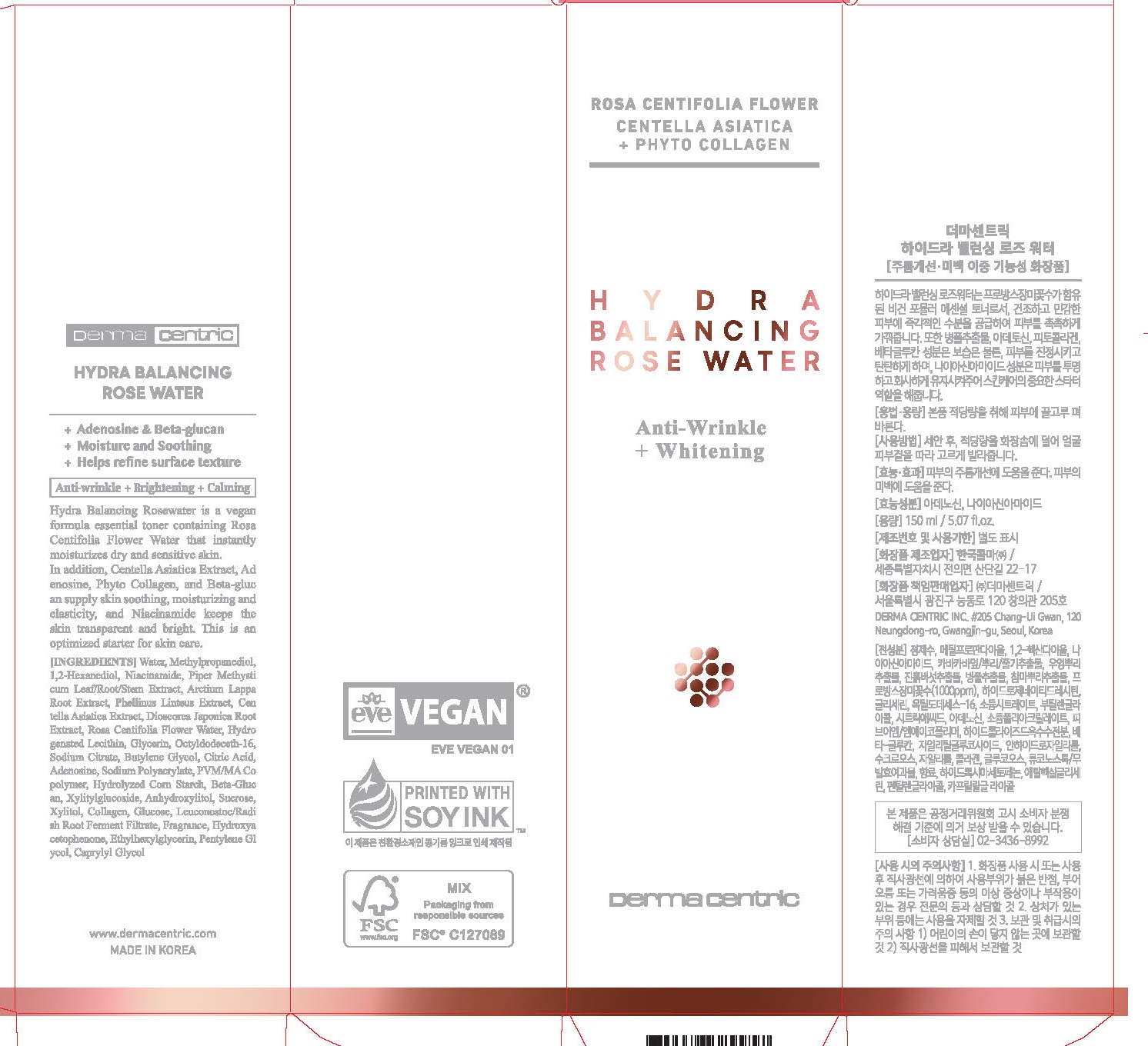 DRUG LABEL: HYDRA BALANCING ROSE WATER
NDC: 79593-0009 | Form: LIQUID
Manufacturer: DERMA CENTRIC INC
Category: otc | Type: HUMAN OTC DRUG LABEL
Date: 20210328

ACTIVE INGREDIENTS: ADENOSINE 0.044 g/100 mL; NIACINAMIDE 2 g/100 mL
INACTIVE INGREDIENTS: WATER; GLYCERIN

ACTIVE INGREDIENT

niacinamide, adenosine

PURPOSE

anti wrinkle

brightening

calming

KEEP OUT OF REACH OF THE CHILDREN

WARNINGS

■ For external use only.

■ Do not use in eyes.

■ lf swallowed, get medical help promptly.

■ Stop use, ask doctor lf irritation occurs.

■ Keep out of reach of children.

DOSAGE AND ADMINISTRATION

for external use only

INACTIVE INGREDIENT

WATER
METHYLPROPANEDIOL
1,2-HEXANEDIOL
NIACINAMIDE
GLYCERIN
BUTYLENE GLYCOL
OCTYLDODECETH-16
HYDROXYACETOPHENONE
SODIUM CITRATE
ROSA CENTIFOLIA FLOWER WATER
CITRIC ACID
ETHYLHEXYLGLYCERIN
ADENOSINE
FRAGRANCE
DIOSCOREA JAPONICA ROOT EXTRACT
PVM/MA COPOLYMER
SODIUM POLYACRYLATE
HYDROGENATED LECITHIN
HYDROLYZED CORN STARCH
PIPER METHYSTICUM LEAF/ROOT/STEM EXTRACT
ARCTIUM LAPPA ROOT EXTRACT
BETA-GLUCAN
PHELLINUS LINTEUS EXTRACT
XYLITYLGLUCOSIDE
ANHYDROXYLITOL
SUCROSE
XYLITOL
CENTELLA ASIATICA EXTRACT
PENTYLENE GLYCOL
PHENOXYETHANOL
COLLAGEN
GLUCOSE
CAPRYLYL GLYCOL
LEUCONOSTOC/RADISH ROOT FERMENT FILTRATE
TOCOPHEROL

WATER
METHYLPROPANEDIOL
1,2-HEXANEDIOL
NIACINAMIDE
GLYCERIN
BUTYLENE GLYCOL
OCTYLDODECETH-16
HYDROXYACETOPHENONE
SODIUM CITRATE
ROSA CENTIFOLIA FLOWER WATER
CITRIC ACID
ETHYLHEXYLGLYCERIN
ADENOSINE
FRAGRANCE
DIOSCOREA JAPONICA ROOT EXTRACT
PVM/MA COPOLYMER
SODIUM POLYACRYLATE
HYDROGENATED LECITHIN
HYDROLYZED CORN STARCH
PIPER METHYSTICUM LEAF/ROOT/STEM EXTRACT
ARCTIUM LAPPA ROOT EXTRACT
BETA-GLUCAN
PHELLINUS LINTEUS EXTRACT
XYLITYLGLUCOSIDE
ANHYDROXYLITOL
SUCROSE
XYLITOL
CENTELLA ASIATICA EXTRACT
PENTYLENE GLYCOL
PHENOXYETHANOL
COLLAGEN
GLUCOSE
CAPRYLYL GLYCOL
LEUCONOSTOC/RADISH ROOT FERMENT FILTRATE
TOCOPHEROL

INDICATIONS AND USAGE

apply proper amount to the skin